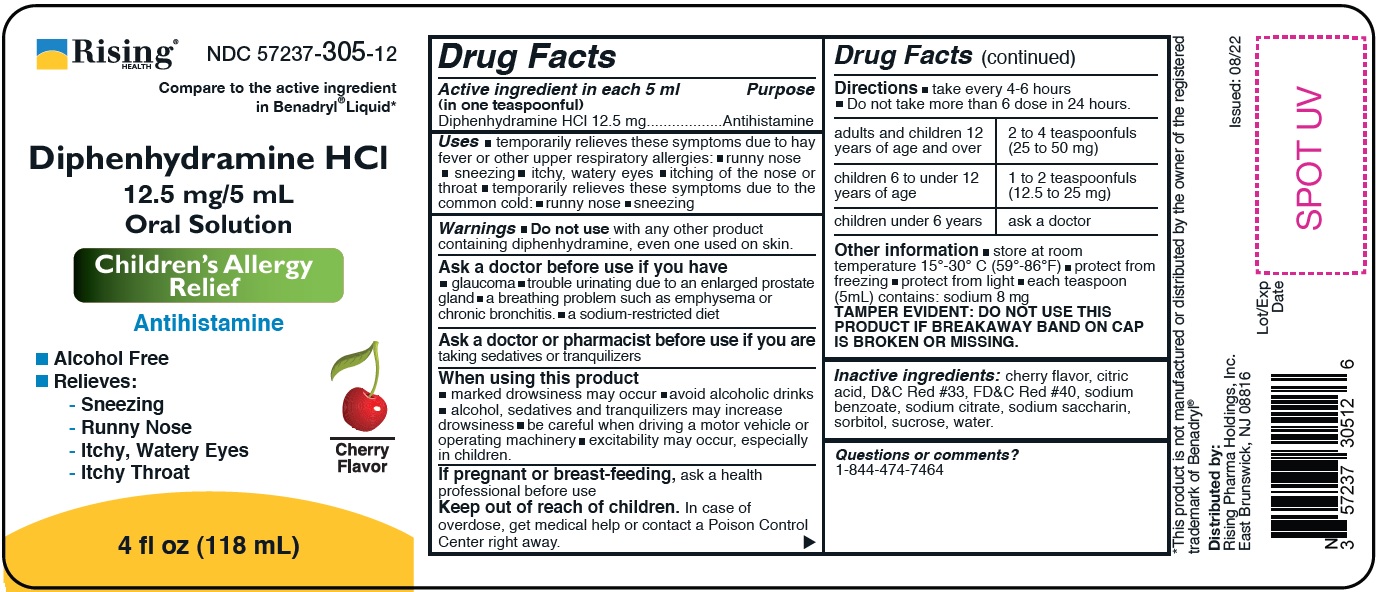 DRUG LABEL: Diphenhydramine Oral Liquid
NDC: 57237-305 | Form: LIQUID
Manufacturer: Rising Pharma Holdings, Inc.
Category: otc | Type: HUMAN OTC DRUG LABEL
Date: 20241018

ACTIVE INGREDIENTS: Diphenhydramine Hydrochloride 12.5 mg/5 mL
INACTIVE INGREDIENTS: Anhydrous Citric Acid; D&C RED NO. 33 ; FD&C RED NO. 40  ; Sodium Benzoate; Sodium Citrate; Saccharin Sodium; Sorbitol; Sucrose; Water

Drug Facts

Active ingredient in each 5 mL (in one teaspoonful)

Diphenhydramine HCl, 12.5 mg

Purpose

Antihistamine

Uses

temporarily relieves these symptoms due to hay fever or other upper respiratory allergies:

- runny nose
- sneezing
- itchy, watery eyes
- itching of the nose or throat

temporarily relieves these symptoms due to the common cold:

- runny nose
- sneezing

Warnings

Do not use

- with any other product containing diphenhydramine, even one used on skin.

Ask a doctor before use if you have

- glaucoma
- trouble urinating due to an enlarged prostate gland
- a breathing problem such as emphysema or chronic bronchitis.
- a sodium-restricted diet

Ask a doctor or pharmacist before use if you are taking sedatives or tranquilizers.

When using this product

- marked drowsiness may occur
- avoid alcoholic drinks
- alcohol, sedatives and tranquilizers may increase drowsiness
- be careful when driving a motor vehicle or operating machinery
- excitability may occur, especially in children.

If pregnant or breast-feeding,

ask a health professional before use

Keep out of reach of children.

In case of overdose, get medical help or contact a Poison Control Center right away.

Directions

- take every 4-6 hours
- Do not use more than 6 dose in 24 hours

adults and children 12 years of age and over | 2 to 4 teaspoonfuls (25 to 50 mg)
children 6 to under 12 years of age | 1 to 2 teaspoonfuls (12.5 to 25 mg)
children under 6 years | ask a doctor

Other information

- store at room temperature 15º - 30ºC (59º - 86ºF)
- protect from freezing
- protect from light
- each teaspoon (5 mL) contains: sodium 8 mg

TAMPER EVIDENT: DO NOT USE THIS PRODUCT IF BREAKAWAY BAND ON CAP IS BROKEN OR MISSING.

Inactive ingredients

cherry flavor, citric acid, D & C Red #33, FD & C Red #40, flavor, sodium benzoate, sodium citrate, sodium saccharin, sorbitol, sucrose, water.

Questions or comments?

1-844-474-7464

PRINCIPAL DISPLAY PANEL

Rising Health, LLC

NDC 57237-305-12

Diphenhydramine Hcl 12.5 mg/5 mL Oral Solution

4 fl oz (118 mL)